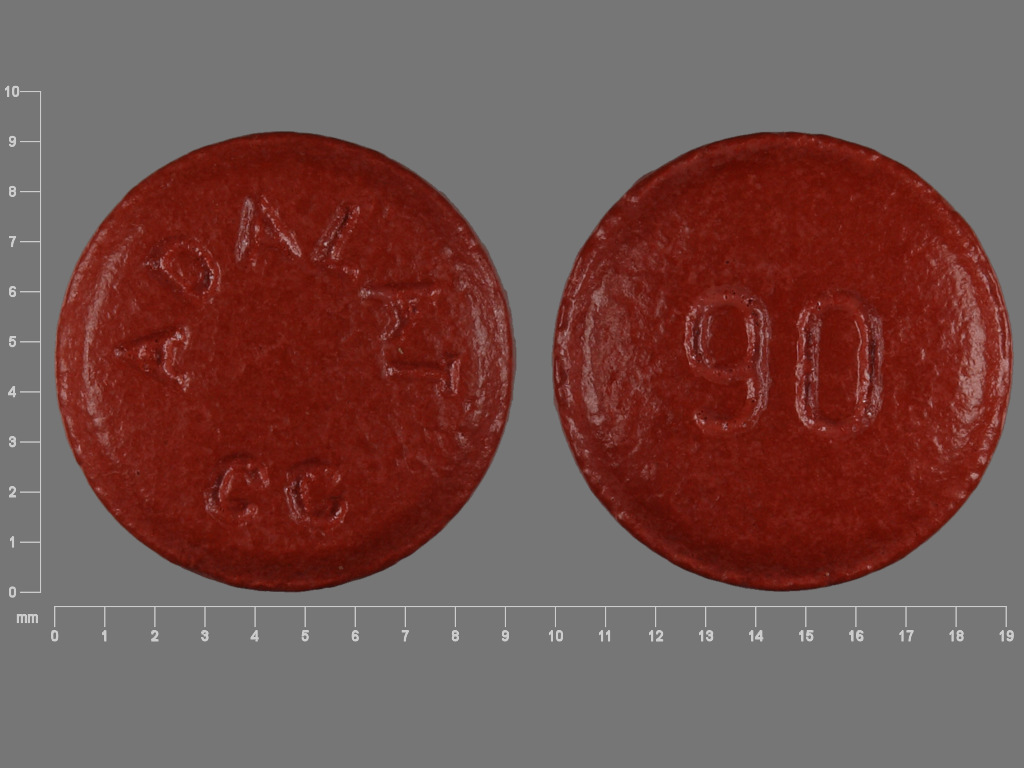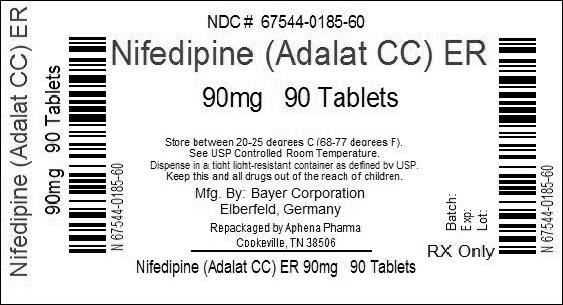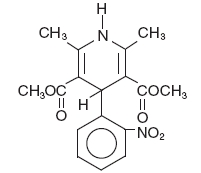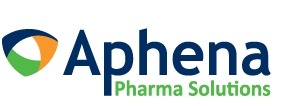 DRUG LABEL: Adalat CC
NDC: 67544-185 | Form: TABLET, FILM COATED
Manufacturer: Aphena Pharma Solutions - Tennessee, LLC
Category: prescription | Type: HUMAN PRESCRIPTION DRUG LABEL
Date: 20140514

ACTIVE INGREDIENTS: NIFEDIPINE 90 mg/1 1
INACTIVE INGREDIENTS: CELLULOSE, MICROCRYSTALLINE; CROSPOVIDONE; FERRIC OXIDE RED; HYDROXYPROPYL CELLULOSE; HYPROMELLOSES; LACTOSE; MAGNESIUM STEARATE; POLYETHYLENE GLYCOLS; SILICON DIOXIDE; STARCH, CORN; TITANIUM DIOXIDE

ADALAT®CC
(nifedipine)
Extended Release Tablets
For Oral Use

DESCRIPTION

Adalat® CC is an extended release tablet dosage form of the calcium channel blocker nifedipine. Nifedipine is 3,5-pyridinedicarboxylic acid, 1,4-dihydro-2,6-dimethyl-4-(2-nitrophenyl)-dimethyl ester, C17H18N2O6, and has the structural formula:

Nifedipine is a yellow crystalline substance, practically insoluble in water but soluble in ethanol. It has a molecular weight of 346.3. Adalat CC tablets consist of an external coat and an internal core. Both contain nifedipine, the coat as a slow release formulation and the core as a fast release formulation. Adalat CC tablets contain either: 30, 60, or 90 mg of nifedipine for once-a-day oral administration.

Inert ingredients in the formulation are: hydroxypropylcellulose, lactose, corn starch, crospovidone, microcrystalline cellulose, silicon dioxide, and magnesium stearate. The inert ingredients in the film coating for Adalat CC 30 and 60 are: hypromellose, polyethylene glycol, ferric oxide, and titanium dioxide. The inert ingredients in the film coating for Adalat CC 90 are: hypromellose, polyethylene glycol and ferric oxide

CLINICAL PHARMACOLOGY

Nifedipine is a calcium ion influx inhibitor (slow-channel blocker or calcium ion antagonist) which inhibits the transmembrane influx of calcium ions into vascular smooth muscle and cardiac muscle. The contractile processes of vascular smooth muscle and cardiac muscle are dependent upon the movement of extracellular calcium ions into these cells through specific ion channels. Nifedipine selectively inhibits calcium ion influx across the cell membrane of vascular smooth muscle and cardiac muscle without altering serum calcium concentrations.

Mechanism of Action

The mechanism by which nifedipine reduces arterial blood pressure involves peripheral arterial vasodilatation and, consequently, a reduction in peripheral vascular resistance. The increased peripheral vascular resistance, an underlying cause of hypertension, results from an increase in active tension in the vascular smooth muscle. Studies have demonstrated that the increase in active tension reflects an increase in cytosolic free calcium.

Nifedipine is a peripheral arterial vasodilator which acts directly on vascular smooth muscle. The binding of nifedipine to voltage-dependent and possibly receptor-operated channels in vascular smooth muscle results in an inhibition of calcium influx through these channels. Stores of intracellular calcium in vascular smooth muscle are limited and thus dependent upon the influx of extracellular calcium for contraction to occur. The reduction in calcium influx by nifedipine causes arterial vasodilation and decreased peripheral vascular resistance which results in reduced arterial blood pressure.

Pharmacokinetics and Metabolism

Nifedipine is completely absorbed after oral administration. The bioavailability of nifedipine as Adalat CC relative to immediate release nifedipine is in the range of 84%-89%. After ingestion of Adalat CC tablets under fasting conditions, plasma concentrations peak at about 2.5-5 hours with a second small peak or shoulder evident at approximately 6-12 hours post dose. The elimination half-life of nifedipine administered as Adalat CC is approximately 7 hours in contrast to the known 2 hour elimination half-life of nifedipine administered as an immediate release capsule.

When Adalat CC is administered as multiples of 30 mg tablets over a dose range of 30 mg to 90 mg, the area under the curve (AUC) is dose proportional; however, the peak plasma concentration for the 90 mg dose given as 3 x 30 mg is 29% greater than predicted from the 30 mg and 60 mg doses.

Two 30 mg Adalat CC tablets may be interchanged with a 60 mg Adalat CC tablet. Three 30 mg Adalat CC tablets, however, result in substantially higher Cmax values than those after a single 90 mg Adalat CC tablet. Three 30 mg tablets should, therefore, not be considered interchangeable with a 90 mg tablet.

Once daily dosing of Adalat CC under fasting conditions results in decreased fluctuations in the plasma concentration of nifedipine when compared to t.i.d. dosing with immediate release nifedipine capsules. The mean peak plasma concentration of nifedipine following a 90 mg Adalat CC tablet, administered under fasting conditions, is approximately 115 ng/mL. When Adalat CC is given immediately after a high fat meal in healthy volunteers, there is an average increase of 60% in the peak plasma nifedipine concentration, a prolongation in the time to peak concentration, but no significant change in the AUC. Plasma concentrations of nifedipine when Adalat CC is taken after a fatty meal result in slightly lower peaks compared to the same daily dose of the immediate release formulation administered in three divided doses. This may be, in part, because Adalat CC is less bioavailable than the immediate release formulation.

Nifedipine is extensively metabolized to highly water soluble, inactive metabolites accounting for 60% to 80% of the dose excreted in the urine. Only traces (less than 0.1% of the dose) of the unchanged form can be detected in the urine. The remainder is excreted in the feces in metabolized form, most likely as a result of biliary excretion.

Nifedipine is metabolized via the cytochrome P450 3A4 system. Drugs that are known to either inhibit or induce this enzyme system may alter the first pass or clearance of nifedipine.

No studies have been performed with Adalat CC in patients with renal failure; however, significant alterations in the pharmacokinetics of nifedipine immediate release capsules have not been reported in patients undergoing hemodialysis or chronic ambulatory peritoneal dialysis. Since the absorption of nifedipine from Adalat CC could be modified by renal disease, caution should be exercised in treating such patients.

Because nifedipine is metabolized via the cytochrome P450 3A4 system, its pharmacokinetics may be altered in patients with chronic liver disease. Adalat CC has not been studied in patients with hepatic disease; however, in patients with hepatic impairment (liver cirrhosis) nifedipine has a longer elimination half-life and higher bioavailability than in healthy volunteers.

The degree of protein binding of nifedipine is high (92%-98%). Protein binding may be greatly reduced in patients with renal or hepatic impairment.

After administration of Adalat CC to healthy elderly men and women (age > 60 years), the mean Cmax is 36% higher and the average plasma concentration is 70% greater than in younger patients.

In healthy subjects, the elimination half-life of a different sustained release nifedipine formulation was longer in elderly subjects (6.7 h) compared to young subjects (3.8 h) following oral administration. A decreased clearance was also observed in the elderly (348 mL/min) compared to young subjects (519 mL/min) following intravenous administration.

Co-administration of nifedipine with grapefruit juice results in up to a 2-fold increase in AUC and Cmax, due to inhibition of CYP3A related first-pass metabolism. Ingestion of grapefruit and grapefruit juice should be avoided while taking nifedipine.

Clinical Studies

Adalat CC produced dose-related decreases in systolic and diastolic blood pressure as demonstrated in two double-blind, randomized, placebo-controlled trials in which over 350 patients were treated with Adalat CC 30, 60 or 90 mg once daily for 6 weeks. In the first study, Adalat CC was given as monotherapy and in the second study, Adalat CC was added to a beta-blocker in patients not controlled on a beta-blocker alone. The mean trough (24 hours post-dose) blood pressure results from these studies are shown below:

MEAN REDUCTIONS IN TROUGH SUPINE BLOOD PRESSURE (mmHg)
SYSTOLIC/DIASTOLIC
 | STUDY 1
ADALAT CC | N | MEAN TROUGH
DOSE |  | REDUCTION [Placebo response subtracted.]
30 MG | 60 | 5.3/2.9
60 MG | 57 | 8.0/4.1
90 MG | 55 | 12.5/8.1
 | STUDY 2
ADALAT CC | N | MEAN TROUGH
DOSE |  | REDUCTION*
30 MG | 58 | 7.6/3.8
60 MG | 63 | 10.1/5.3
90 MG | 62 | 10.2/5.8

The trough/peak ratios estimated from 24 hour blood pressure monitoring ranged from 41%-78% for diastolic and 46%-91% for systolic blood pressure.

Hemodynamics

Like other slow-channel blockers, nifedipine exerts a negative inotropic effect on isolated myocardial tissue. This is rarely, if ever, seen in intact animals or man, probably because of reflex responses to its vasodilating effects. In man, nifedipine decreases peripheral vascular resistance which leads to a fall in systolic and diastolic pressures, usually minimal in normotensive volunteers (less than 5-10 mm Hg systolic), but sometimes larger. With Adalat CC, these decreases in blood pressure are not accompanied by any significant change in heart rate. Hemodynamic studies of the immediate release nifedipine formulation in patients with normal ventricular function have generally found a small increase in cardiac index without major effects on ejection fraction, left ventricular end-diastolic pressure (LVEDP) or volume (LVEDV). In patients with impaired ventricular function, most acute studies have shown some increase in ejection fraction and reduction in left ventricular filling pressure.

Electrophysiologic Effects

Although, like other members of its class, nifedipine causes a slight depression of sinoatrial node function and atrioventricular conduction in isolated myocardial preparations, such effects have not been seen in studies in intact animals or in man. In formal electrophysiologic studies, predominantly in patients with normal conduction systems, nifedipine administered as the immediate release capsule has had no tendency to prolong atrioventricular conduction or sinus node recovery time, or to slow sinus rate.

INDICATION AND USAGE

Adalat CC is indicated for the treatment of hypertension. It may be used alone or in combination with other antihypertensive agents.

CONTRAINDICATIONS

Concomitant administration with strong P450 inducers, such as rifampin, are contraindicated since the efficacy of nifedipine tablets could be significantly reduced. (See PRECAUTIONS, Drug Interactions.)

Nifedipine must not be used in cases of cardiogenic shock.

Adalat is contraindicated in patients with a known hypersensitivity to any component of the tablet.

WARNINGS

Excessive Hypotension

Although in most patients the hypotensive effect of nifedipine is modest and well tolerated, occasional patients have had excessive and poorly tolerated hypotension. These responses have usually occurred during initial titration or at the time of subsequent upward dosage adjustment, and may be more likely in patients using concomitant beta-blockers.

Severe hypotension and/or increased fluid volume requirements have been reported in patients who received immediate release capsules together with a beta-blocking agent and who underwent coronary artery bypass surgery using high dose fentanyl anesthesia. The interaction with high dose fentanyl appears to be due to the combination of nifedipine and a beta-blocker, but the possibility that it may occur with nifedipine alone, with low doses of fentanyl, in other surgical procedures, or with other narcotic analgesics cannot be ruled out. In nifedipine-treated patients where surgery using high dose fentanyl anesthesia is contemplated, the physician should be aware of these potential problems and, if the patient’s condition permits, sufficient time (at least 36 hours) should be allowed for nifedipine to be washed out of the body prior to surgery.

Increased Angina and/or Myocardial Infarction

Rarely, patients, particularly those who have severe obstructive coronary artery disease, have developed well-documented increased frequency, duration and/or severity of angina or acute myocardial infarction upon starting nifedipine or at the time of dosage increase. The mechanism of this effect is not established.

Beta-Blocker Withdrawal

When discontinuing a beta-blocker it is important to taper its dose, if possible, rather than stopping abruptly before beginning nifedipine. Patients recently withdrawn from beta blockers may develop a withdrawal syndrome with increased angina, probably related to increased sensitivity to catecholamines. Initiation of nifedipine treatment will not prevent this occurrence and on occasion has been reported to increase it.

Congestive Heart Failure

Rarely, patients (usually while receiving a beta-blocker) have developed heart failure after beginning nifedipine. Patients with tight aortic stenosis may be at greater risk for such an event, as the unloading effect of nifedipine would be expected to be of less benefit to these patients, owing to their fixed impedance to flow across the aortic valve.

PRECAUTIONS

General

Hypotension

Because nifedipine decreases peripheral vascular resistance, careful monitoring of blood pressure during the initial administration and titration of Adalat CC is suggested. Close observation is especially recommended for patients already taking medications that are known to lower blood pressure (See WARNINGS).

Peripheral Edema

Mild to moderate peripheral edema occurs in a dose-dependent manner with Adalat CC. The placebo subtracted rate is approximately 8% at 30 mg, 12% at 60 mg and 19% at 90 mg daily. This edema is a localized phenomenon, thought to be associated with vasodilation of dependent arterioles and small blood vessels and not due to left ventricular dysfunction or generalized fluid retention. With patients whose hypertension is complicated by congestive heart failure, care should be taken to differentiate this peripheral edema from the effects of increasing left ventricular dysfunction.

Use in Cirrhotic Patients

Clearance of nifedipine is reduced and systemic exposure increased in patients with cirrhosis. It is unknown how systemic exposure may be altered in patients with moderate or severe liver impairment. Careful monitoring and dose reduction may be necessary; consider initiating therapy with the lowest dose available.

Information for Patients

Adalat CC is an extended release tablet and should be swallowed whole and taken on an empty stomach. It should not be administered with food. Do not chew, divide or crush tablets.

Laboratory Tests

Rare, usually transient, but occasionally significant elevations of enzymes such as alkaline phosphatase, CPK, LDH, SGOT, and SGPT have been noted. The relationship to nifedipine therapy is uncertain in most cases, but probable in some. These laboratory abnormalities have rarely been associated with clinical symptoms; however, cholestasis with or without jaundice has been reported. A small increase (<5%) in mean alkaline phosphatase was noted in patients treated with Adalat CC. This was an isolated finding and it rarely resulted in values which fell outside the normal range. Rare instances of allergic hepatitis have been reported with nifedipine treatment. In controlled studies, Adalat CC did not adversely affect serum uric acid, glucose, cholesterol or potassium.

Nifedipine, like other calcium channel blockers, decreases platelet aggregation in vitro. Limited clinical studies have demonstrated a moderate but statistically significant decrease in platelet aggregation and increase in bleeding time in some nifedipine patients. This is thought to be a function of inhibition of calcium transport across the platelet membrane. No clinical significance for these findings has been demonstrated.

Positive direct Coombs’ test with or without hemolytic anemia has been reported but a causal relationship between nifedipine administration and positivity of this laboratory test, including hemolysis, could not be determined.

Although nifedipine has been used safely in patients with renal dysfunction and has been reported to exert a beneficial effect in certain cases, rare reversible elevations in BUN and serum creatinine have been reported in patients with pre-existing chronic renal insufficiency. The relationship to nifedipine therapy is uncertain in most cases but probable in some.

Drug Interactions

Nifedipine is mainly eliminated by metabolism and is a substrate of CYP3A. Inhibitors and inducers of CYP3A can impact the exposure to nifedipine and consequently its desirable and undesirable effects. In vitro and in vivo data indicate that nifedipine can inhibit the metabolism of drugs that are substrates of CYP3A, thereby increasing the exposure to other drugs. Nifedipine is a vasodilator, and co-administration of other drugs affecting blood pressure may result in pharmacodynamic interactions.

CYP3A inhibitors

CYP3A inhibitors such as ketoconazole, fluconazole, itraconazole, clarithromycin, erythromycin (Azithromycin, although structurally related to the class of macrolide antibiotic is void of clinically relevant CYP3A4 inhibition), grapefruit, nefazodone, fluoxetine, saquinavir, indinavir, nelfinavir, and ritonavir may result in increased exposure to nifedipine when co-administered. Careful monitoring and dose adjustment may be necessary; consider initiating nifedipine at the lowest dose available if given concomitantly with these medications.

Strong CYP3A inducers, such as rifampin, rifabutin, phenobarbital, phenytoin, carbamazepine, and St. John’s Wort reduce the bioavailability and efficacy of nifedipine; therefore nifedipine should not be used in combination with strong CYP3A inducers such as rifampin (See CONTRAINDICATIONS).

Cardiovascular Drugs

Antiarrhythmics

Quinidine: Quinidine is a substrate of CYP3A and has been shown to inhibit CYP3A in vitro. Co-administration of multiple doses of quinidine sulfate, 200 mg t.i.d., and nifedipine, 20 mg t.i.d., increased Cmax and AUC of nifedipine in healthy volunteers by factors of 2.30 and 1.37, respectively. The heart rate in the initial interval after drug administration was increased by up to 17.9 beats/minute. The exposure to quinidine was not importantly changed in the presence of nifedipine. Monitoring of heart rate and adjustment of the nifedipine dose, if necessary, are recommended when quinidine is added to a treatment with nifedipine.

Flecainide: There has been too little experience with the co-administration of Tambocor with nifedipine to recommend concomitant use.

Calcium Channel Blockers

Diltiazem: Pre-treatment of healthy volunteers with 30 mg or 90 mg t.i.d. diltiazem p.o. increased the AUC of nifedipine after a single dose of 20 mg nifedipine by factors of 2.2 and 3.1, respectively. The corresponding Cmax values of nifedipine increased by factors of 2.0 and 1.7, respectively. Caution should be exercised when co-administering diltiazem and nifedipine and a reduction of the dose of nifedipine should be considered.

Verapamil: Verapamil, a CYP3A inhibitor, can inhibit the metabolism of nifedipine and increase the exposure to nifedipine during concomitant therapy. Blood pressure should be monitored and reduction of the dose of nifedipine considered.

ACE Inhibitors

Benazepril: In healthy volunteers receiving single dose of 20 mg nifedipine ER and benazepril 10 mg, the plasma concentrations of benazeprilat and nifedipine in the presence and absence of each other were not statistically significantly different. A hypotensive effect was only seen after co-administration of the two drugs. The tachycardic effect of nifedipine was attenuated in the presence of benazepril.

Angiotensin-II Blockers

Irbesartan: In vitro studies show significant inhibition of the formation of oxidized irbesartan metabolites by nifedipine. However, in clinical studies, concomitant nifedipine had no effect on irbesartan pharmacokinetics.

Candesartan: No significant drug interaction has been reported in studies with candesartan cilexitil given together with nifedipine. Because candesartan is not significantly metabolized by the cytochrome P450 system and at therapeutic concentrations has no effect on cytochrome P450 enzymes, interactions with drugs that inhibit or are metabolized by those enzymes would not be expected.

Beta-blockers

Adalat CC was well tolerated when administered in combination with beta-blockers in 187 hypertensive patients in a placebo-controlled clinical trial. However, there have been occasional literature reports suggesting that the combination nifedipine and beta-adrenergic blocking drugs may increase the likelihood of congestive heart failure, severe hypotension or exacerbation of angina in patients with cardiovascular disease. Clinical monitoring is recommended and a dose adjustment of nifedipine should be considered.

Timolol: Hypotension is more likely to occur if dihydropryridine calcium antagonists such as nifedipine are co-administered with timolol.

Central Alpha1-Blockers

Doxazosin: Healthy volunteers participating in a multiple dose doxazosin-nifedipine interaction study received 2 mg doxazosin q.d. alone or combined with 20 mg nifedipine ER b.i.d. Co-administration of nifedipine resulted in a decrease in AUC and Cmax of doxazosin to 83% and 86% of the values in the absence of nifedipine, respectively. In the presence of doxazosin, AUC and Cmax of nifedipine were increased by factors of 1.13 and 1.23, respectively. Compared to nifedipine monotherapy, blood pressure was lower in the presence of doxazosin. Blood pressure should be monitored when doxazosin is co-administered with nifedipine, and dose reduction of nifedipine considered.

Digitalis

Digoxin: The simultaneous administration of nifedipine and digoxin may lead to reduced clearance resulting in an increase in plasma concentrations of digoxin. Since there have been isolated reports of patients with elevated digoxin levels, and there is a possible interaction between digoxin and Adalat CC, it is recommended that digoxin levels be monitored when initiating, adjusting and discontinuing Adalat CC to avoid possible over- or under- digitalization.

Antithrombotics

Coumarins: There have been rare reports of increased prothrombin time in patients taking coumarin anticoagulants to whom nifedipine was administered. However the relationship to nifedipine therapy is uncertain.

Platelet Aggregation Inhibitors

Clopidogrel: No clinically significant pharmacodynamic interactions were observed when clopidrogrel was co-administered with nifedipine.

Tirofiban: Co-administration of nifedipine did not alter the exposure to tirofiban importantly.

Other

Diuretics, PDE5 inhibitors, alpha-methyldopa: Nifedipine may increase the blood pressure lowering effect of these concomitantly administered agents.

Non-Cardiovascular Drugs

Antifungal Drugs

Ketoconazole, itraconazole and fluconazole are CYP3A inhibitors and can inhibit the metabolism of nifedipine and increase the exposure to nifedipine during concomitant therapy. Blood pressure should be monitored and a dose reduction of nifedipine considered.

Antisecretory Drugs

Omeprazole: In healthy volunteers receiving a single dose of 10 mg nifedipine, AUC and Cmax of nifedipine after pretreatment with omeprazole 20 mg q.d. for 8 days were 1.26 and 0.87 times those after pre-treatment with placebo. Pretreatment with or co-administration of omeprazole did not impact the effect of nifedipine on blood pressure or heart rate. The impact of omeprazole on nifedipine is not likely to be of clinical relevance.

Pantoprazole: In healthy volunteers the exposure to neither drug was changed significantly in the presence of the other drug.

Ranitidine: Five studies in healthy volunteers investigated the impact of multiple ranitidine doses on the single or multiple dose pharmacokinetics of nifedipine. Two studies investigated the impact of co-administered ranitidine on blood pressure in hypertensive subjects on nifedipine. Co-administration of ranitidine did not have relevant effects on the exposure to nifedipine that affected the blood pressure or heart rate in normotensive or hypertensive subjects.

Cimetidine: Five studies in healthy volunteers investigated the impact of multiple cimetidine doses on the single or multiple dose pharmacokinetics of nifedipine. Two studies investigated the impact of co-administered cimetidine on blood pressure in hypertensive subjects on nifedipine. In normotensive subjects receiving single doses of 10 mg or multiple doses of up to 20 mg nifedipine t.i.d. alone or together with cimetidine up to 1000 mg/day, the AUC values of nifedipine in the presence of cimetidine were between 1.52 and 2.01 times those in the absence of cimetidine. The Cmax values of nifedipine in the presence of cimetidine were increased by factors ranging between 1.60 and 2.02. The increase in exposure to nifedipine by cimetidine was accompanied by relevant changes in blood pressure or heart rate in normotensive subjects. Hypertensive subjects receiving 10 mg q.d. nifedipine alone or in combination with cimetidine 1000 mg q.d. also experienced relevant changes in blood pressure when cimetidine was added to nifedipine. The interaction between cimetidine and nifedipine is of clinical relevance and blood pressure should be monitored and a reduction of the dose of nifedipine considered.

Cisapride: Simultaneous administration of cisapride and nifedipine may lead to increased plasma concentrations of nifedipine.

Antibacterial Drugs

Quinupristin/Dalfopristin: In vitro drug interaction studies have demonstrated that quinupristin/dalfopristin significantly inhibits the CYP3A metabolism of nifedipine. Concomitant administration of quinupristin/dalfopristin and nifedipine (repeated oral dose) in healthy volunteers increased AUC and Cmax for nifedipine by factors of 1.44 and 1.18, respectively, compared to nifedipine monotherapy. Upon co-administration of quinupristin/dalfopristin with nifedipine, blood pressure should be monitored and a reduction of the dose of nifedipine considered.

Erythromycin: Erythromycin, a CYP3A inhibitor, can inhibit the metabolism of nifedipine and increase the exposure to nifedipine during concomitant therapy. Blood pressure should be monitored and reduction of the dose of nifedipine considered.

Antitubercular Drugs

Rifampin: Strong CYP3A inducers, such as rifampin, rifapentin, and rifabutin reduce the bioavailability of nifedipine which may reduce the efficacy of nifedipine; therefore nifedipine should not be used in combination with strong CYP3A inducers such as rifampin (See CONTRAINDICATIONS). The impact of multiple oral doses of 600 mg rifampin on the pharmacokinetics of nifedipine after a single oral dose of 20 mg nifedipine capsule was evaluated in a clinical study. Twelve healthy male volunteers received a single oral dose of 20 mg nifedipine capsule on study Day 1. Starting on study Day 2, the subjects received 600 mg rifampin once daily for 14 days. On study Day 15, a second single oral dose of 20 mg nifedipine capsule was administered together with the last dose of rifampin. Compared to study Day 1, 14 days pretreatment with rifampin reduced Cmaxand AUC of concomitantly administered nifedipine on average by 95% and 97%, respectively.

Antiviral Drugs

Amprenavir, atanazavir, delavirine, fosamprinavir, indinavir, nelfinavir and ritonavir, as CYP3A inhibitors, can inhibit the metabolism of nifedipine and increase the exposure to nifedipine. Caution is warranted and clinical monitoring of patients recommended.

CNS Drugs

Nefazodone, a CYP3A inhibitor, can inhibit the metabolism of nifedipine and increase the exposure to nifedipine during concomitant therapy. Blood pressure should be monitored and a reduction of the dose of nifedipine considered.

Fluoxetine, a CYP3A inhibitor, can inhibit the metabolism of nifedipine and increase the exposure to nifedipine during concomitant therapy. Blood pressure should be monitored and a reduction of the dose of nifedipine considered.

Valproic acid may increase the exposure to nifedipine during concomitant therapy. Blood pressure should be monitored and a dose reduction of nifedipine considered.

Phenytoin, Phenobarbital, and Carbamazepine: Nifedipine is metabolized by CYP3A. Co-administration of nifedipine 10 mg capsule and 60 mg nifedipine coat-core tablet with phenytoin, an inducer of CYP3A, lowered the AUC and Cmax of nifedipine by approximately 70%. Phenobarbital and carbamazepine are also inducers of CYP3A. Alternative antihypertensive therapy should be considered in patients taking phenytoin, phenobarbital, and carbamazepine.

Antiemetic Drugs

Dolasetron: In patients taking dolasetron by the oral or intravenous route and nifedipine, no effect was shown on the clearance of hydrodolasetron.

Immunosuppressive Drugs

Tacrolimus: Tacrolimus has been shown to be metabolized via the CYP3A system. Nifedipine has been shown to inhibit the metabolism of tacrolimus in vitro. Transplant patients on tacrolimus and nifedipine required from 26% to 38% smaller doses than patients not receiving nifedipine. Nifedipine can increase the exposure to tacrolimus. When nifedipine is co-administered with tacrolimus the blood concentrations of tacrolimus should be monitored and a reduction of the dose of tacrolimus considered.

Sirolimus: A single 60 mg dose of nifedipine and a single 10 mg dose of sirolimus oral solution were administered to 24 healthy volunteers. Clinically significant pharmacokinetic drug interactions were not observed.

Glucose Lowering Drugs

Pioglitazone: Co-administration of pioglitazone for 7 days with 30 mg nifedipine ER administered orally q.d. for 4 days to male and female volunteers resulted in least square mean (90% CI) values for unchanged nifedipine of 0.83 (0.73-0.95) for Cmax and 0.88 (0.80-0.96) for AUC relative to nifedipine monotherapy. In view of the high variability of nifedipine pharmacokinetics, the clinical significance of this finding is unknown.

Rosiglitazone: Co-administration of rosiglitazone (4 mg b.i.d.) was shown to have no clinically relevant effect on the pharmacokinetics of nifedipine.

Metformin: A single dose metformin-nifedipine interaction study in normal healthy volunteers demonstrated that co-administration of nifedipine increased plasma metformin Cmax and AUC by 20% and 9%, respectively, and increased the amount of metformin excreted in urine. Tmax and half-life were unaffected. Nifedipine appears to enhance the absorption of metformin.

Miglitol: No effect of miglitol was observed on the pharmacokinetics and pharmacodynamics of nifedipine.

Repaglinide: Co-administration of 10 mg nifedipine with a single dose of 2 mg repaglinide (after 4 days nifedipine 10 mg t.i.d. and repaglinide 2 mg t.i.d.) resulted in unchanged AUC and Cmax values for both drugs.

Acarbose: Nifedipine tends to produce hyperglycemia and may lead to loss of glucose control. If nifedipine is co-administered with acarbose, blood glucose levels should be monitored carefully and a dose adjustment of nifedipine considered.

Drugs Interfering with Food Absorption

Orlistat: In 17 normal-weight subjects receiving orlistat 120 mg t.i.d. for 6 days, orlistat did not alter the bioavailability of 60 mg nifedipine (extended release tablets).

Dietary Supplements

Grapefruit Juice: In healthy volunteers, a single dose co-administration of 250 mL double strength grapefruit juice with 10 mg nifedipine increased AUC and Cmax by factors of 1.35 and 1.13, respectively. Ingestion of repeated doses of grapefruit juice (5 x 200 mL in 12 hours) after administration of 20 mg nifedipine ER increased AUC and Cmax of nifedipine by a factor of 2. Grapefruit juice should be avoided by patients on nifedipine. The intake of grapefruit juice should be stopped at least 3 days prior to initiating patients on nifedipine.

Herbals

St. John’s Wort: St. John’s Wort is an inducer of CYP3A and may decrease exposure to nifedipine. Alternative antihypertensive therapy should be considered in patients in whom St. John’s Wort therapy is necessary.

CYP2D6 Probe Drug

Debrisoquine: In healthy volunteers, pretreatment with nifedipine 20 mg t.i.d. for 5 days did not change the metabolic ratio of hydroxydebrisoquine to debrisoquine measured in urine after a single dose of 10 mg debrisoquine. Thus, it is improbable that nifedipine inhibits in vivo the metabolism of other drugs that are substrates of CYP2D6.

Carcinogenesis, Mutagenesis, Impairment of Fertility

Nifedipine was administered orally to rats for two years and was not shown to be carcinogenic. When given to rats prior to mating, nifedipine caused reduced fertility at a dose approximately 30 times the maximum recommended human dose. There is a literature report of reversible reduction in the ability of human sperm obtained from a limited number of infertile men taking recommended doses of nifedipine to bind to and fertilize an ovum in vitro. In vivo mutagenicity studies were negative.

Pregnancy

Pregnancy Category C.

In rodents, rabbits and monkeys, nifedipine has been shown to have a variety of embryotoxic, placentotoxic, teratogenic and fetotoxic effects, including stunted fetuses (rats, mice and rabbits), digital anomalies (rats and rabbits), rib deformities (mice), cleft palate (mice), small placentas and underdeveloped chorionic villi (monkeys), embryonic and fetal deaths (rats, mice and rabbits), prolonged pregnancy (rats; not evaluated in other species), and decreased neonatal survival (rats; not evaluated in other species). On a mg/kg or mg/m^2 basis, some of the doses associated with these various effects are higher than the maximum recommended human dose and some are lower, but all are within an order of magnitude of it.

The digital anomalies seen in nifedipine-exposed rabbit pups are strikingly similar to those seen in pups exposed to phenytoin, and these are in turn similar to the phalangeal deformities that are the most common malformation seen in human children with in utero exposure to phenytoin.

From the clinical evidence available, a specific prenatal risk has not been identified. However, an increase in perinatal asphyxia, caesarean delivery, prematurity and intrauterine growth retardation have been reported.

Careful monitoring of blood pressure must be exercised in pregnant women, when administering nifedipine in combination with IV magnesium sulfate due to the possibility of an excessive fall in blood pressure which could harm the mother and fetus.

There are no adequate and well-controlled studies in pregnant women.

Nursing Mothers

Nifedipine is excreted in human milk. Nursing mothers are advised not to breastfeed their babies when taking the drug.

Pediatric Use

The safety and effectiveness of Adalat CC in pediatric patients have not been established.

Geriatric Use

Although small pharmacokinetic studies have identified an increased half-life and increased Cmax and AUC (See CLINICAL PHARMACOLOGY: Pharmacokinetics and Metabolism), clinical studies of nifedipine did not include sufficient numbers of subjects aged 65 and over to determine whether they respond differently from younger subjects. Other reported clinical experience has not identified differences in responses between the elderly and younger patients. In general, dose selection for an elderly patient should be cautious, usually starting at the low end of the dosing range, reflecting the greater frequency of decreased hepatic, renal, or cardiac function, and of concomitant disease or other drug therapy.

Patients with Galactose Intolerance

Since this medicinal product contains lactose, patients with rare hereditary problems of galactose intolerance, the Lapp lactase deficiency or glucose-galactose malabsorption should not take this medicine.

ADVERSE EXPERIENCES

The incidence of adverse events during treatment with Adalat CC in doses up to 90 mg daily were derived from multi-center placebo-controlled clinical trials in 370 hypertensive patients. Atenolol 50 mg once daily was used concomitantly in 187 of the 370 patients on Adalat CC and in 64 of the 126 patients on placebo. All adverse events reported during Adalat CC therapy were tabulated independently of their causal relationship to medication.

The most common adverse event reported with Adalat CC was peripheral edema. This was dose related and the frequency was 18% on Adalat CC 30 mg daily, 22% on Adalat CC 60 mg daily and 29% on Adalat CC 90 mg daily versus 10% on placebo.

Other common adverse events reported in the above placebo-controlled trials include:

 | ADALAT CC (%) | PLACEBO (%)
 | (n=370) | (n=126)
Adverse Event
Headache | 19 | 13
Flushing/heat sensation | 4 | 0
Dizziness | 4 | 2
Fatigue/asthenia | 4 | 4
Nausea | 2 | 1
Constipation | 1 | 0

Where the frequency of adverse events with Adalat CC and placebo is similar, causal relationship cannot be established.

The following adverse events were reported with an incidence of 3% or less in daily doses up to 90 mg:

Body as a Whole/Systemic: chest pain, leg pain

Central Nervous System: paresthesia, vertigo

Dermatologic: rash

Gastrointestinal: constipation

Musculoskeletal: leg cramps

Respiratory: epistaxis, rhinitis

Urogenital: impotence, urinary frequency

Other adverse events reported with an incidence of less than 1.0% were:

Body as a Whole/Systemic: allergic reaction, asthenia, cellulitis, substernal chest pain, chills, facial edema, lab test abnormal, malaise, neck pain, pelvic pain, pain, photosensitivity reaction

Cardiovascular: atrial fibrillation, bradycardia, cardiac arrest, extrasystole, hypotension, migraine, palpitations, phlebitis, postural hypotension, tachycardia, cutaneous angiectases

Central Nervous System: anxiety, confusion, decreased libido, depression, hypertonia, hypesthesia, insomnia, somnolence

Dermatologic: angioedema, petechial rash, pruritus, sweating

Gastrointestinal: abdominal pain, diarrhea, dry mouth, dysphagia, dyspepsia, eructation, esophagitis, flatulence, gastrointestinal disorder, gastrointestinal hemorrhage, GGT increased, gum disorder, gum hemorrhage, vomiting

Hematologic: eosinophilia, lymphadenopathy

Metabolic: gout, weight loss

Musculoskeletal: arthralgia, arthritis, joint disorder, myalgia, myasthenia

Respiratory: dyspnea, increased cough, rales, pharyngitis, stridor

Special Senses: abnormal vision, amblyopia, conjunctivitis, diplopia, eye disorder, eye hemorrhage, tinnitus

Urogenital/Reproductive: dysuria, kidney calculus, nocturia, breast engorgement, polyuria, urogenital disorder, erectile dysfunction (ED)

The following adverse events have been reported rarely in patients given nifedipine in coat core or other formulations: allergenic hepatitis, alopecia, anaphylactic reaction, anemia, arthritis with ANA (+), depression, erythromelalgia, exfoliative dermatitis, fever, gingival hyperplasia, gynecomastia, hyperglycemia, jaundice, leukopenia, mood changes, muscle cramps, nervousness, paranoid syndrome, purpura, shakiness, sleep disturbances, Stevens-Johnson syndrome, syncope, taste perversion, thrombocytopenia, toxic epidermal necrolysis, transient blindness at the peak of plasma level, tremor and urticaria.

OVERDOSAGE

Experience with nifedipine overdosage is limited. Symptoms associated with severe nifedipine overdosage include loss of consciousness, drop in blood pressure, heart rhythm disturbances, metabolic acidosis, hypoxia, cardiogenic shock with pulmonary edema. Generally, overdosage with nifedipine leading to pronounced hypotension calls for active cardiovascular support including monitoring of cardiovascular and respiratory function, elevation of extremities, judicious use of calcium infusion, pressor agents and fluids. After oral ingestion, thorough gastric lavage is indicated, if necessary in combination with irrigation of the small intestine. In cases involving overdosage of a slow-release product like nifedipine, elimination must be as complete as possible, including from the small intestine, to prevent the subsequent absorption of the active substance. Additional liquid or volume must be administered with caution because of the risk of fluid overload.

Clearance of nifedipine would be expected to be prolonged in patients with impaired liver function. Since nifedipine is highly protein bound, dialysis is not likely to be of any benefit; however, plasmapheresis may be beneficial.

There has been one reported case of massive overdosage with tablets of another extended release formulation of nifedipine. The main effects of ingestion of approximately 4800 mg of nifedipine in a young man attempting suicide as a result of cocaine-induced depression was initial dizziness, palpitations, flushing, and nervousness. Within several hours of ingestion, nausea, vomiting, and generalized edema developed. No significant hypotension was apparent at presentation, 18 hours post ingestion. Blood chemistry abnormalities consisted of a mild, transient elevation of serum creatinine, and modest elevations of LDH and CPK, but normal SGOT. Vital signs remained stable, no electrocardiographic abnormalities were noted and renal function returned to normal within 24 to 48 hours with routine supportive measures alone. No prolonged sequelae were observed.

The effect of a single 900 mg ingestion of nifedipine capsules in a depressed anginal patient on tricyclic antidepressants was loss of consciousness within 30 minutes of ingestion, and profound hypotension, which responded to calcium infusion, pressor agents, and fluid replacement. A variety of ECG abnormalities were seen in this patient with a history of bundle branch block, including sinus bradycardia and varying degrees of AV block. These dictated the prophylactic placement of a temporary ventricular pacemaker, but otherwise resolved spontaneously. Significant hyperglycemia was seen initially in this patient, but plasma glucose levels rapidly normalized without further treatment.

A young hypertensive patient with advanced renal failure ingested 280 mg of nifedipine capsules at one time, with resulting marked hypotension responding to calcium infusion and fluids. No AV conduction abnormalities, arrhythmias, or pronounced changes in heart rate were noted, nor was there any further deterioration in renal function.

Bradycardiac heart rhythm disturbances may be treated symptomatically with ß-sympathomimetics, and in life-threatening bradycardiac disturbances of heart rhythm temporary pacemaker therapy can be advisable.

DOSAGE AND ADMINISTRATION

Dosage should be adjusted according to each patient’s needs. It is recommended that Adalat CC be administered orally once daily on an empty stomach. Adalat CC is an extended release dosage form and tablets should be swallowed whole, not bitten or divided. In general, titration should proceed over a 7-14 day period starting with 30 mg once daily. Upward titration should be based on therapeutic efficacy and safety. The usual maintenance dose is 30 mg to 60 mg once daily. Titration to doses above 90 mg daily is not recommended.

If discontinuation of Adalat CC is necessary, sound clinical practice suggests that the dosage should be decreased gradually with close physician supervision.

Co-administration of nifedipine with grapefruit juice is to be avoided (See CLINICAL PHARMACOLOGY and PRECAUTIONS).

Care should be taken when dispensing Adalat CC to assure that the extended release dosage form has been prescribed.

HOW SUPPLIED

Repackaged by Aphena Pharma Solutions - TN.
See Repackaging Information for available configurations.

Adalat CC extended release tablets are supplied as 30 mg, 60 mg, and 90 mg round film coated tablets. The different strengths can be identified as follows:

Strength | Color | Markings
30 mg | Pink | 30 on one side and ADALAT CC on the other side
60 mg | Salmon | 60 on one side and ADALAT CC on the other side
90 mg | Dark Red | 90 on one side and ADALAT CC on the other side

Adalat® CC Tablets are supplied in:

 | Strength | NDC Code
Bottles of 100 | 30 mg | 50419-701-05
 | 60 mg | 50419-702-05
 | 90 mg | 50419-703-05
Bottles of 1000 | 30 mg | 50419-701-10
 | 60 mg | 50419-702-10

The tablets should be protected from light and moisture and stored below 86°F (30°C). Dispense in tight, light-resistant containers.

Manufactured for:

Bayer HealthCare Pharmaceuticals Inc.
Wayne, NJ 07470
Manufactured in Germany

Adalat is a registered trademark of Bayer Aktiengesellschaft.

Rx Only

©2011 Bayer HealthCare Pharmaceuticals Inc. Printed in U.S.A.

The following are representative examples of ADALAT labeling. See the "How Supplied" section for a complete listing of all components.

Repackaging Information

Please reference the How Supplied section listed above for a description of individual tablets or capsules. This drug product has been received by Aphena Pharma - TN in a manufacturer or distributor packaged configuration and repackaged in full compliance with all applicable cGMP regulations. The package configurations available from Aphena are listed below:

Count | 90mg
90 | 67544-185-60
800 | 67544-185-81
1200 | 67544-185-82

Store between 20°-25°C (68°-77°F). See USP Controlled Room Temperature. Dispense in a tight light-resistant container as defined by USP. Keep this and all drugs out of the reach of children.

Repackaged by:
Cookeville, TN 38506
20140514SC

PRINCIPAL DISPLAY PANEL - 90mg

NDC 67544-185 - Nifedipine (Adalat® CC) ER 90mg - Rx Only